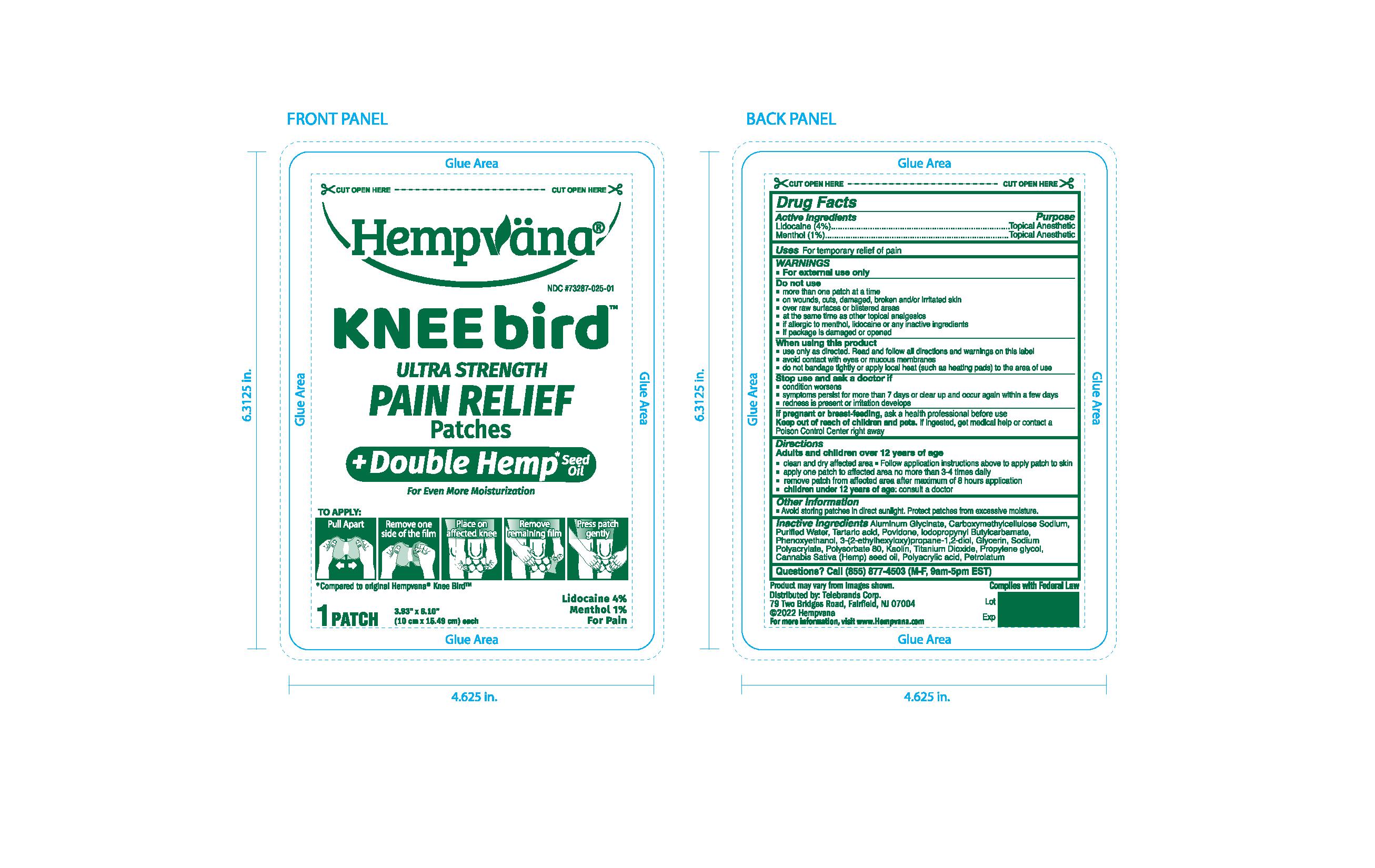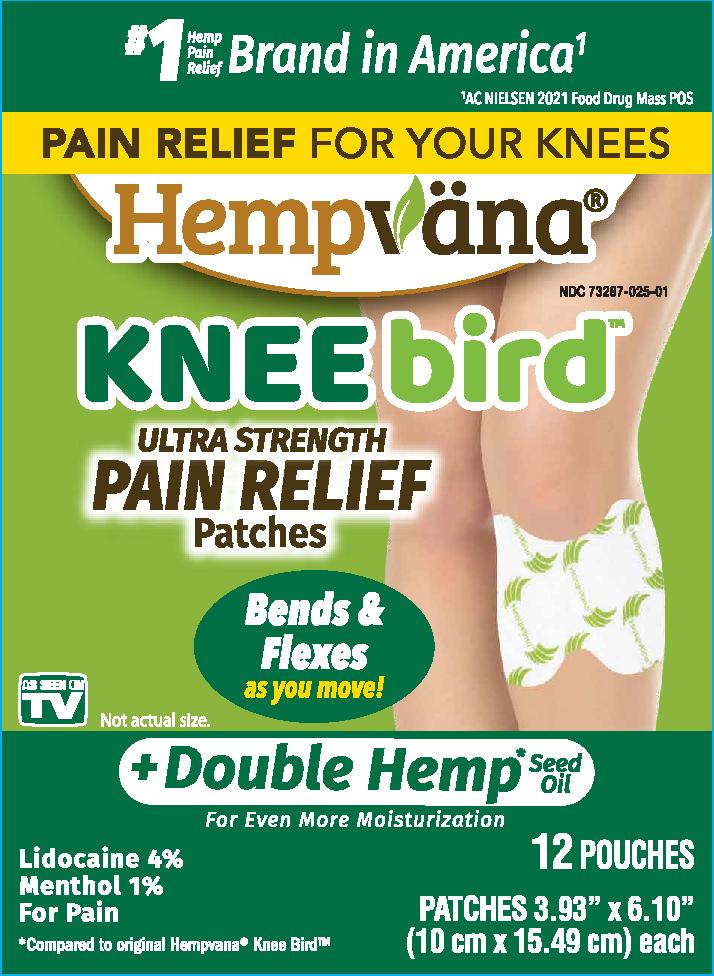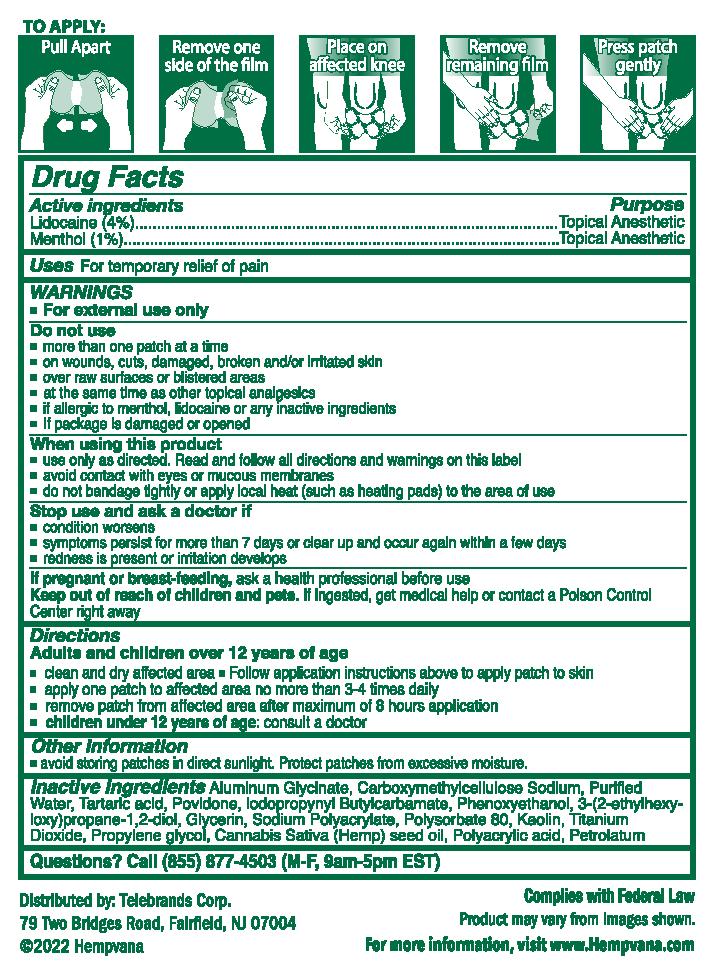 DRUG LABEL: Hempvana Knee Bird Ultra Strength Pain Relief
NDC: 73287-025 | Form: PATCH
Manufacturer: TELEBRANDS CORP
Category: otc | Type: HUMAN OTC DRUG LABEL
Date: 20241120

ACTIVE INGREDIENTS: MENTHOL 1 g/100 g; LIDOCAINE 4 g/100 g
INACTIVE INGREDIENTS: DIHYDROXYALUMINUM AMINOACETATE ANHYDROUS; KAOLIN; POVIDONE; CARBOXYMETHYLCELLULOSE SODIUM; GLYCERIN; SODIUM POLYACRYLATE (2500000 MW); CANNABIS SATIVA SEED OIL; POLYACRYLIC ACID (250000 MW); IODOPROPYNYL BUTYLCARBAMATE; TITANIUM DIOXIDE; POLYSORBATE 80; WATER; PROPYLENE GLYCOL; TARTARIC ACID; ETHYLHEXYLGLYCERIN; PHENOXYETHANOL; PETROLATUM

Hempvana Knee Bird Ultra Strength Pain Relief Patches

Active ingredients

Lidocaine (4%)

Menthol (1%)

Purpose

Lidocaine (4%)..................Topical Anesthetic

Menthol (1%)....................Topical Anesthetic

Uses

For temporary relief of pain

Warnings

For external use only

Do not use

- more than one patch at a time
- on wounds, cuts, damaged, broken and/or irritated skin
- over raw surfaces or blistered areas
- at the same time as other topical analgesics
- if allergic to menthol, lidocaine or any other inactive ingredients
- if package is damaged or opened

When using this product

- use only as directed. Read and follow all directions and warnings on this label
- avoid contact with eyes or mucous membranes
- do not bandage tightly or apply local heat (such as heating pads) to the area of use

Stop use and ask a doctor if

- condition worsens
- symptoms persist for more than 7 days or clear up and occur again within a few days
- redness is present or irritation develops

PREGNANCY OR BREAST FEEDING

If pregnant or breast-feeding,ask a health professional before use

Keep out of reach of children and pets.If ingested, get medical help or contact a Poison Control Center right away

Directions

Adults and children over 12 years of age

- clean and dry affected area
- follow application instructions above to apply patch to skin
- apply one patch to affected area no more than 3-4 times daily
- remove patch from affected area after maximum of 8 hours application
- children under 12 years of age:consult a doctor

Other information

- avoid storing patches in direct sunlight. Protect patches from excessive moisture.

Inactive ingredients

Aluminum Glycinate, Carboxymethylcellulose Sodium, Purified Water, Tartaric acid, Povidone, Iodopropynyl Butylcarbamate, Phenoxyethanol, 3-(2-ethylhexyloxy)propane-1,2-diol, Glycerin, Sodium Polyacrylate, Polysorbate 80, Kaolin, Titanium Dioxide, Propylene Glycol, Cannabis Sativa (Hemp) Seed Oil, Polyacrylic acid, Petrolatum

Questions?

Call (855) 877-4503 (M-F, 9am-5pm EST)

PACKAGE LABEL

#1 Hemp Pain Relief Brand in America^1

^1AC NIELSEN 2021 Food Drug Mass POS

Pain Relief for Your Knees

Hempvana

Kneebird

Ultra Strength Pain RElief Patches

Bends & Flexes as you move!

As Seen on TV

Not actual size

For Even More Moisturization

Lidocaine 4%

Menthol 1%

For Pain

*Compared to original Hempvana Knee Bird

12 Pourches

Patches 3.93"x6.10"

(10cm x 15.49cm) each